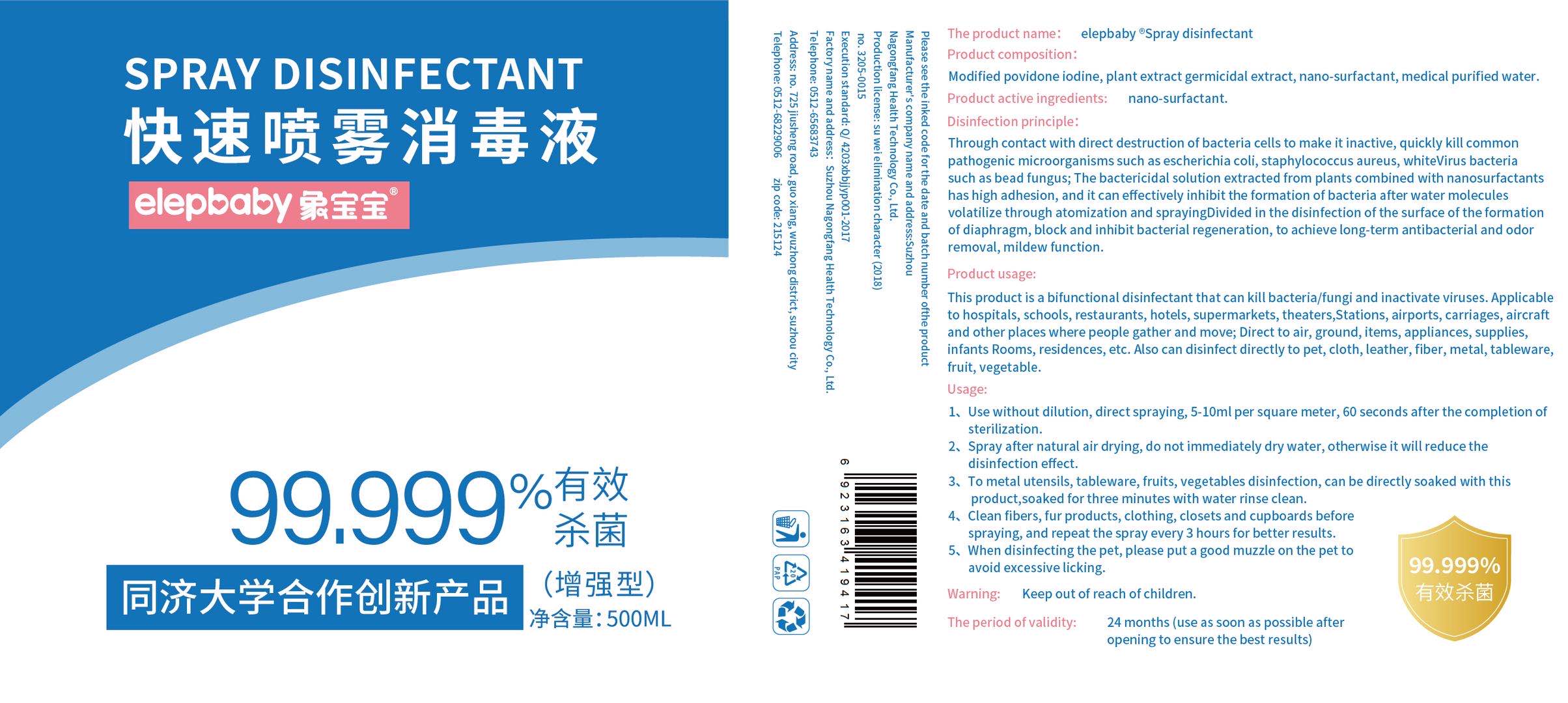 DRUG LABEL: elepbaby disinfectant
NDC: 41506-002 | Form: LIQUID
Manufacturer: Suzhou Nagongfang Health Technology Co., Ltd.
Category: otc | Type: HUMAN OTC DRUG LABEL
Date: 20200508

ACTIVE INGREDIENTS: POVIDONE-IODINE 7.7 mg/500 mL
INACTIVE INGREDIENTS: WATER

ACTIVE INGREDIENT

Modified povidone iodine 0.08-0.3%
plant extract germicidal extract 0.1%

INACTIVE INGREDIENT

medical purified water
nano-surfactant

INDICATIONS AND USAGE

1、Use without dilution, direct spraying, 5- 10ml per square meter, 60 seconds after the completion of sterilization.
2、Spray after natural air drying, do not immediately dry water, otherwise it will reduce the disinfection effect.
3、To metal utensils, tableware, fruits, vegetables disinfection, can be directly soaked with this product,soaked for three minutes with water rinse clean.
4、Clean fibers, fur products, clothing, closets and cupboards before spraying, and repeat the spray every 3 hours for better results.
5、When disinfecting the pet, please put a good muzzle on the pet to avoid excessive licking.

PURPOSE

Disinfection
Sterilization
No Rinseing

keep out of reach of children

keep out of reach of children

DOSAGE AND ADMINISTRATION

It can be pressed for 2-3 times during use, can spray directly on the skin and the surface of the object without drying, and can complete disinfection and sterilization of the hand within 30-60 seconds.